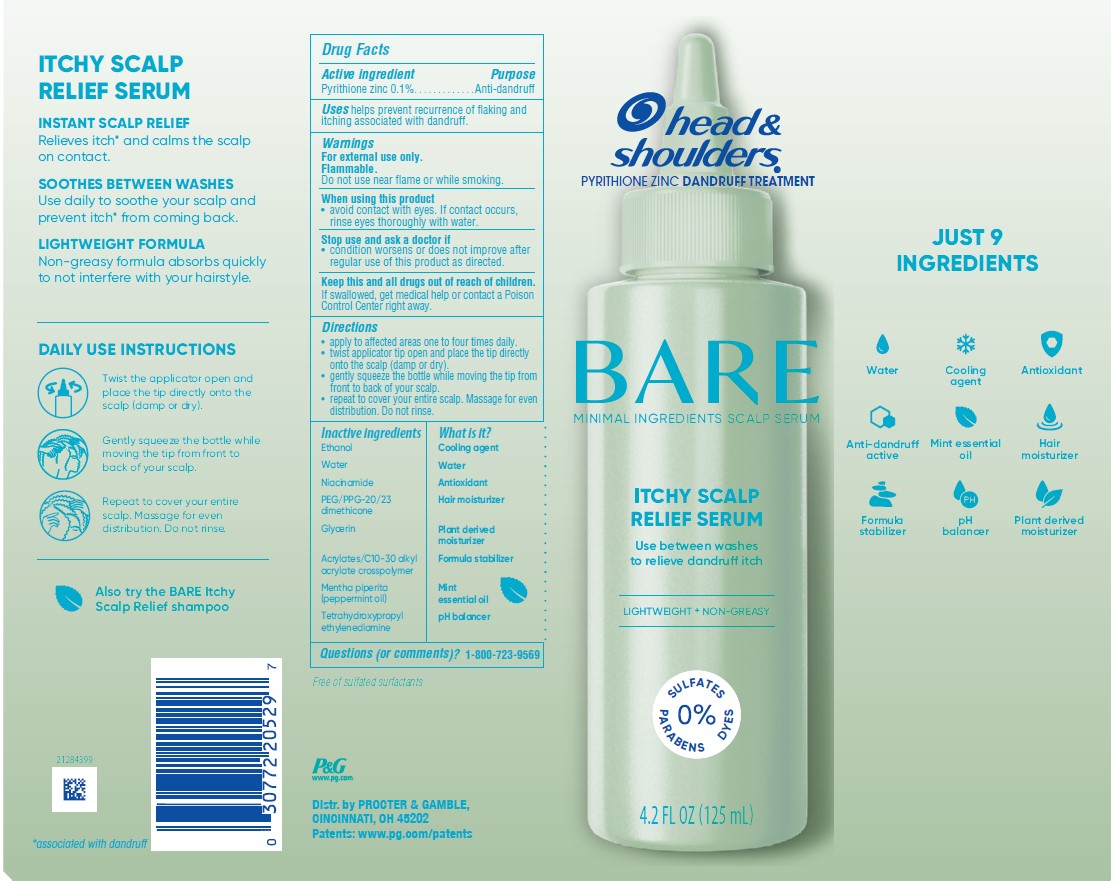 DRUG LABEL: Head and Shoulders Bare Minimal Ingredients Itchy Scalp Relief Serum
NDC: 84126-182 | Form: LIQUID
Manufacturer: The Procter & Gamble Manufacturing Company
Category: otc | Type: HUMAN OTC DRUG LABEL
Date: 20251002

ACTIVE INGREDIENTS: PYRITHIONE ZINC 0.1 g/100 mL
INACTIVE INGREDIENTS: PEG/PPG-20/23 DIMETHICONE; ACRYLATES/C10-30 ALKYL ACRYLATE CROSSPOLYMER (60000 MPA.S); GLYCERIN; MENTHA PIPERITA (PEPPERMINT) OIL; WATER; NIACINAMIDE; ALCOHOL; TETRAHYDROXYPROPYL ETHYLENEDIAMINE

Head and Shoulders Bare Minimal Ingredients Itchy Scalp Relief Serum

Drug Facts

Active ingredient

Pyrithione zinc 0.1%

Purpose

Anti-dandruff

Uses

helps prevent recurrence of flaking and itching associated with dandruff.

Warnings

For external use only.

Flammable.

Do not use near flame or while smoking.

When using this product

- avoid contact with eyes. If contact occurs, rinse eyes thoroughly with water.

Stop use and ask a doctor if

- condition worsens or does not improve after regular use of this product as directed.

KEEP OUT OF REACH OF CHILDREN

Keep this and all drugs out of reach of children. If swallowed, get medical help or contact a Poison Control Center right away.

Directions

• apply to affected areas one to four times daily.
• twist applicator tip open and place the tip directly
onto the scalp (damp or dry).
• gently squeeze the bottle while moving the tip from
front to back of your scalp.
• repeat to cover your entire scalp. Massage for even
distribution. Do not rins

Inactive ingredients

Ethanol
Water
Niacinamide
PEG/PPG-20/23 dimethicone
Glycerin
Acrylates/C10-30 alkyl acrylate crosspolymer
Mentha piperita (peppermint oil)
Tetrahydroxypropyl ethylenediamine

Questions (or comments)?

1-800-723-9569

Dist. by PROCTER & GAMBLE,
CINCINNATI, OH 45202

PRINCIPAL DISPLAY PANEL - 125 mL carton

head &
shoulders®
pyrithione zinc dandruff treatment

BARE

MINIMAL INGREDIENTS SCALP SERUM

ITCHY SCALP

RELIEF SERUM

4.2 FL OZ (125 mL)